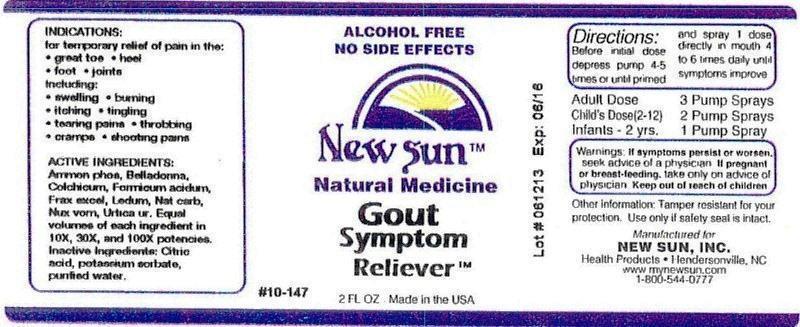 DRUG LABEL: Gout Symptom Reliever
NDC: 66579-0057 | Form: LIQUID
Manufacturer: New Sun Inc.
Category: homeopathic | Type: HUMAN OTC DRUG LABEL
Date: 20140829

ACTIVE INGREDIENTS: AMMONIUM PHOSPHATE, DIBASIC 10 [hp_X]/59 mL; ATROPA BELLADONNA 10 [hp_X]/59 mL; COLCHICUM AUTUMNALE BULB 10 [hp_X]/59 mL; FORMIC ACID 10 [hp_X]/59 mL; FRAXINUS EXCELSIOR BARK 10 [hp_X]/59 mL; FRAXINUS EXCELSIOR LEAF 10 [hp_X]/59 mL; LEDUM PALUSTRE TWIG 10 [hp_X]/59 mL; SODIUM CARBONATE 10 [hp_X]/59 mL; STRYCHNOS NUX-VOMICA SEED 10 [hp_X]/59 mL; URTICA URENS 10 [hp_X]/59 mL
INACTIVE INGREDIENTS: CITRIC ACID MONOHYDRATE; POTASSIUM SORBATE; WATER

Gout Symptom Reliever

DOSAGE AND ADMINISTRATION

Directions: Before initial dose depress pump 4-5 times or until primed and spray 1 dose directly in mouth 4 to 6 times daily until symptoms improve.

Adult Dose: 3 Pump Sprays

Child's Dose (2-12): 2 Pump Sprays

Infants - 2 yrs. 1 Pump Spray

WARNINGS

Warnings: If symptoms persist or worsen, seek advice of physician. If pregnant or breast-feeding, take only on advice of physician.

Keep out of reach of children.

Other information: Tamper resistant for your protection. Use only if safety seal is intact.

PURPOSE

Indications: for temporary relief of pain in the:

- great toe
- heel
- foot
- joints

Including:

- swelling
- burning
- itching
- tingling
- tearing pains
- throbbing
- cramps
- shooting pains

ACTIVE INGREDIENT

Active Ingredients: Ammonium phosphoricum, Belladonna, Colchicum autumnale, Formicum acidum, Fraxinus excelsior, Ledum palustre, Natrum carbonicum, Nux vomica, urtica urens. Equal volumes of each ingredient in 10X, 30X, 100X potencies.

Inactive Ingredient: Citric acid, potassium sorbate, purified water.

Indications: For temporary relief of pain in the:

- great toe
- heel
- foot
- joints

Including:

- swelling
- burning
- itching
- tingling
- tearing pains
- throbbing
- cramps
- shooting pains